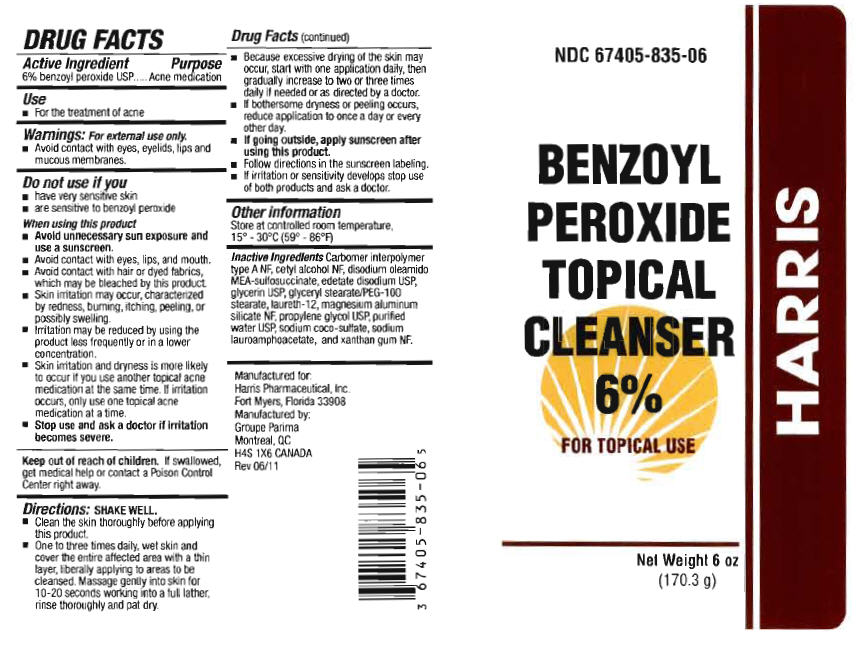 DRUG LABEL: Benzoyl Peroxide
NDC: 67405-835 | Form: LIQUID
Manufacturer: Harris Pharmaceutical, Inc.
Category: otc | Type: HUMAN OTC DRUG LABEL
Date: 20191226

ACTIVE INGREDIENTS: Benzoyl Peroxide 60 mg/1 mL
INACTIVE INGREDIENTS: cetyl alcohol; DISODIUM OLEAMIDO MONOETHANOLAMINE SULFOSUCCINATE; edetate disodium; glycerin; laureth-12; magnesium aluminum silicate; propylene glycol; water; sodium coco-sulfate; sodium lauroamphoacetate; xanthan gum

BENZOYL PEROXIDE TOPICAL CLEANSER 6%

DRUG FACTS

Active Ingredient

6% benzoyl peroxide USP

Purpose

Acne medication

Use

- For the treatment of acne

Warnings:

For external use only.

- Avoid contact with eyes, eyelids, lips and mucous membranes.

Do not use if you

- have very sensitive skin
- are sensitive to benzoyl peroxide

When using this product

- Avoid unnecessary sun exposure and use a sunscreen.
- Avoid contact with eyes, lips, and mouth.
- Avoid contact with hair or dyed fabrics, which may be bleached by this product.
- Skin irritation may occur, characterized by redness, burning, itching, peeling, or possibly swelling.
- Irritation may be reduced by using the product less frequently or in a lower concentration.
- Skin irritation and dryness is more likely to occur if you use another topical acne medication at the same time. If irritation occurs, only use one topical acne medication at a time.

- Stop use and ask a doctor if irritation becomes severe.

Keep out of reach of children

If swallowed, get medical help or contact a Poison Control Center right away.

Directions

SHAKE WELL.

- Clean the skin thoroughly before applying this product.
- One to three times daily, wet skin and cover the entire affected area with a thin layer, liberally applying to areas to be cleansed. Massage gently into skin for 10-20 seconds working into a full lather, rinse thoroughly and pat dry.
- Because excessive drying of the skin may occur, start with one application daily, then gradually increase to two or three times daily if needed or as directed by a doctor.
- If bothersome dryness or peeling occurs, reduce application to once a day or every other day.
- If going outside, apply sunscreen after using this product.
- Follow directions in the sunscreen labeling.
- If irritation or sensitivity develops stop use of both products and ask a doctor.

Other information

Store at controlled room temperature, 15° - 25°C (59° - 77°F)

Inactive Ingredients

Carbomer interpolymer type A NF, cetyl alcohol NF, disodium oleamido MEA-sulfosuccinate, edetate disodium USP, glycerin USP, glyceryl stearate/PEG-100 stearate, laureth-12, magnesium aluminum silicate NF, propylene glycol USP, purified water USP, sodium coco-sulfate, sodium lauroamphoacetate, and xanthan gum NF.

Manufactured for:
Harris Pharmaceutical, Inc.,
Fort Myers, Florida 33908
Manufactured by:
Groupe Parima
Montreal, QC
H4S 1X6 CANADA Rev 06/11

PRINCIPAL DISPLAY PANEL - 170.3 g Bottle Label

NDC 67405-835-06

BENZOYL
PEROXIDE
TOPICAL
CLEANSER
6%

FOR TOPICAL USE

Net Weight 6 oz
(170.3 g)

HARRIS